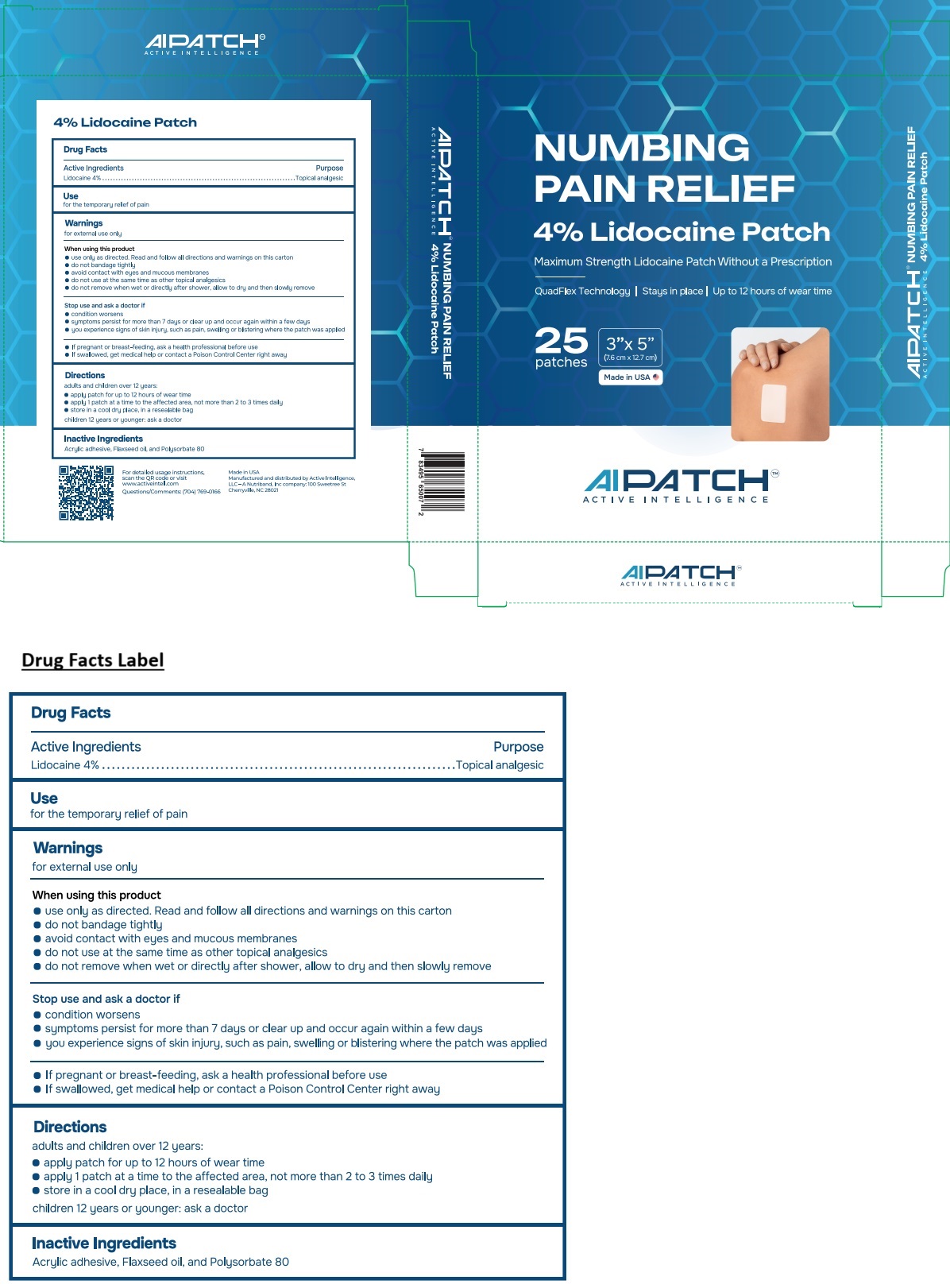 DRUG LABEL: AIPATCH NUMBING PAIN RELIEF
NDC: 71590-012 | Form: PATCH
Manufacturer: Active Intelligence, LLC
Category: otc | Type: HUMAN OTC DRUG LABEL
Date: 20250725

ACTIVE INGREDIENTS: LIDOCAINE 40 mg/1 g
INACTIVE INGREDIENTS: ACRYLIC ACID; LINSEED OIL; POLYSORBATE 80

AIPATCH NUMBING PAIN RELIEF Patch

Active Ingredients

Lidocaine 4%

Purpose

Topical analgesic

Use

for the temporary relief of pain

Warnings

for external use only

When using this product
• use only as directed. Read and follow all directions and warnings on this carton
• do not bandage tightly
• avoid contact with eyes and mucous membranes
• do not use at the same time as other topical analgesics
• do not remove when wet or directly after shower, allow to dry and then slowly remove

Stop use and ask a doctor if
• condition worsens
• symptoms persist for more than 7 days or clear up and occur again within a few days
• you experience signs of skin injury, such as pain, swelling or blistering where the patch was applied

• If pregnant or breast-feeding, ask a health professional before use

KEEP OUT OF REACH OF CHILDREN

• If swallowed, get medical help or contact a Poison Control Center right away

Directions

adults and children over 12 years:
• apply patch for up to 12 hours of wear time
• apply 1 patch at a time to the affected area, not more than 2 to 3 times daily
• store in a cool dry place, in a resealable bag

children 12 years or younger: ask a doctor

Inactive Ingredients

Acrylic adhesive, Flaxseed oil, and Polysorbate 80

Maximum Strength Lidocaine Patch Without a Prescription

QuadFlex Technology | Stays in place | Up to 12 hours of wear time

Made in USA

AIPATCHTM

For detailed usage instructions, scan the QR code or visit www.activeintell.com

Questions/Comments: (704) 769-0166

Manufactured and distributed by Active Intelligence,
LLC -A Nutriband, Inc company: 100 Sweetree St
Cherryville, NC 28021